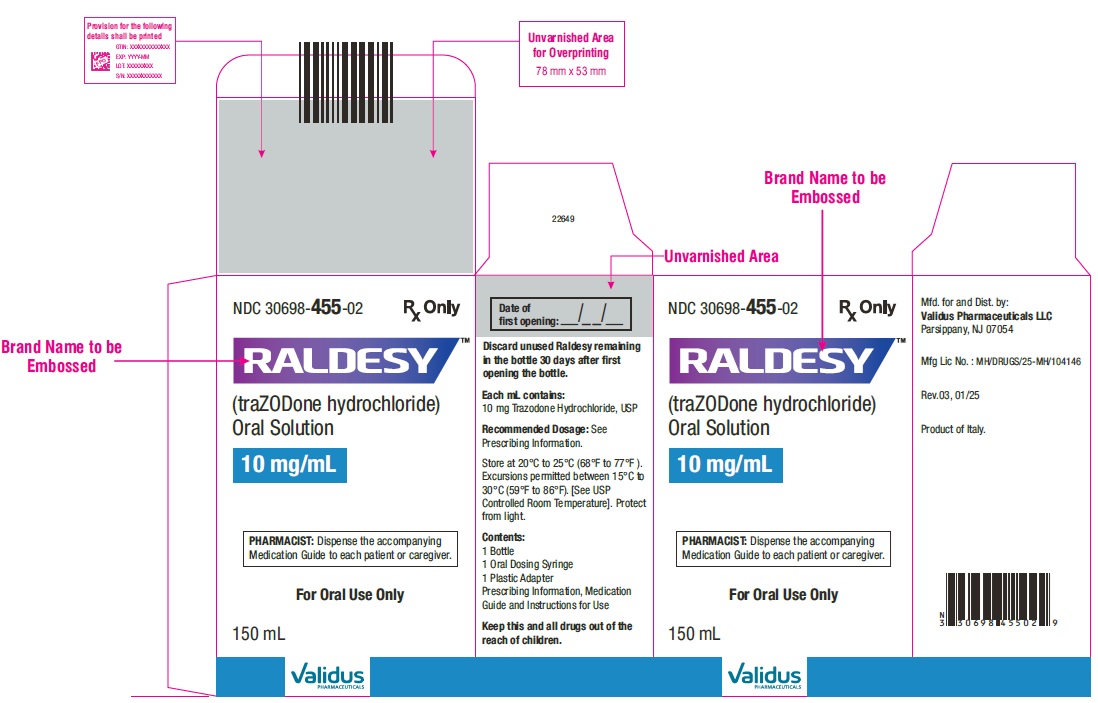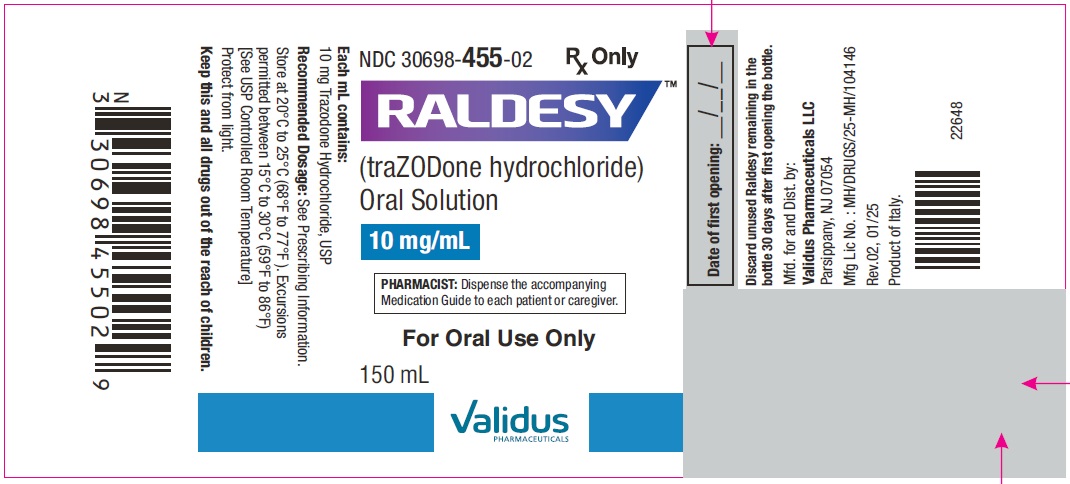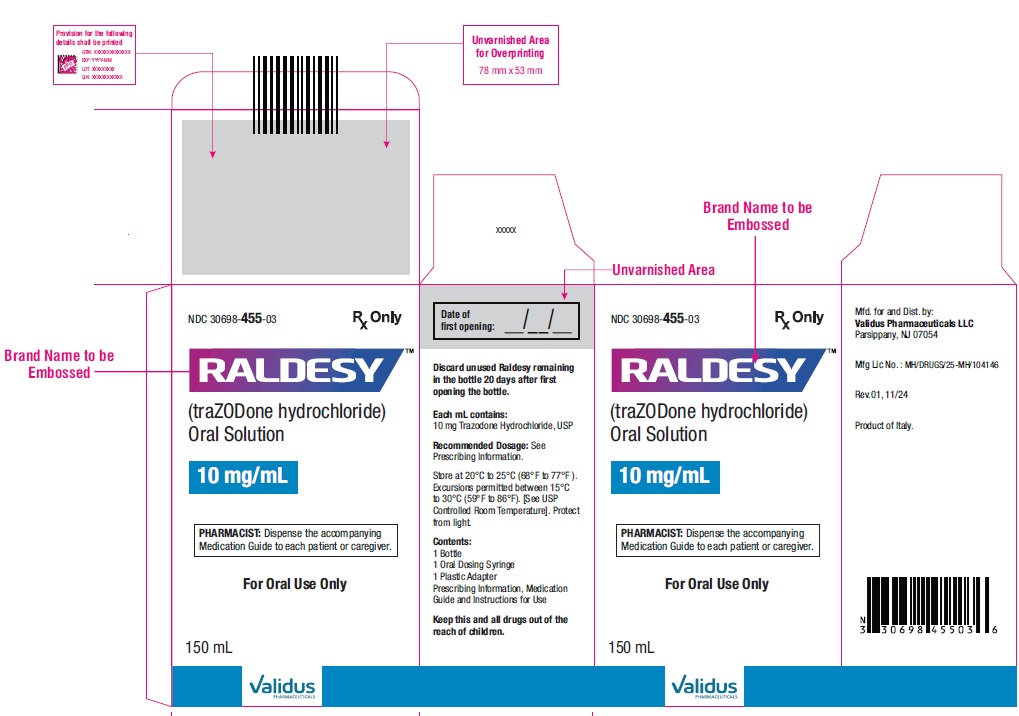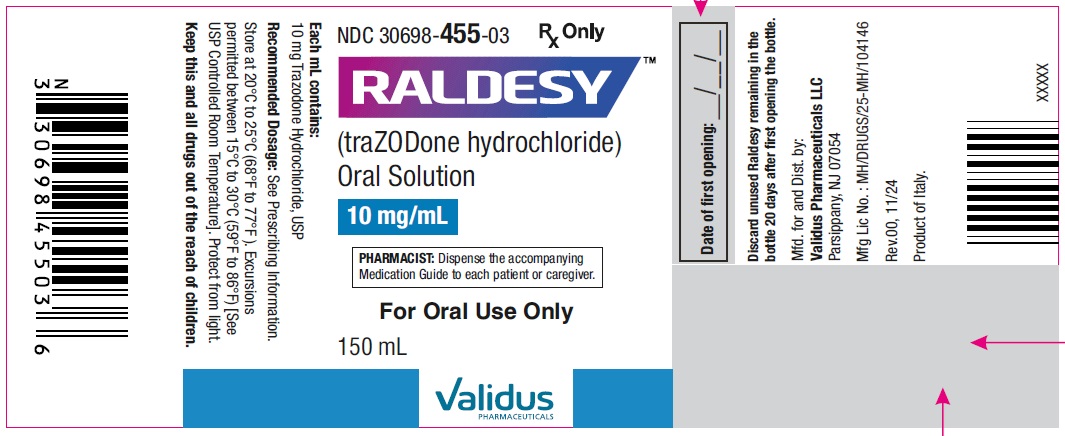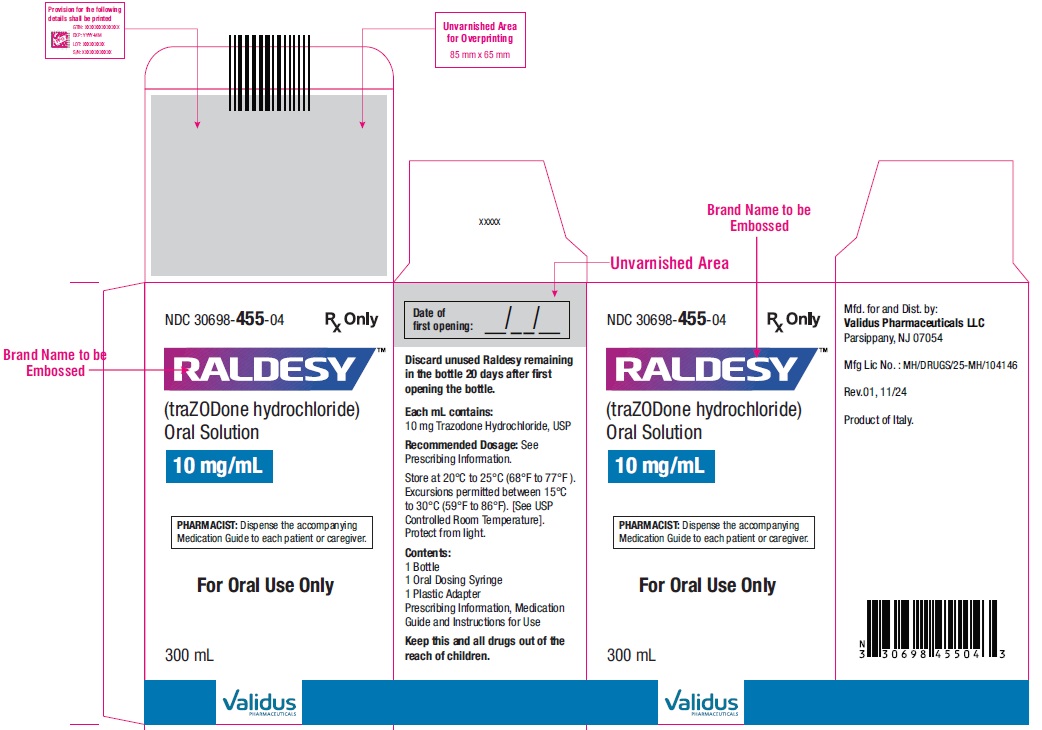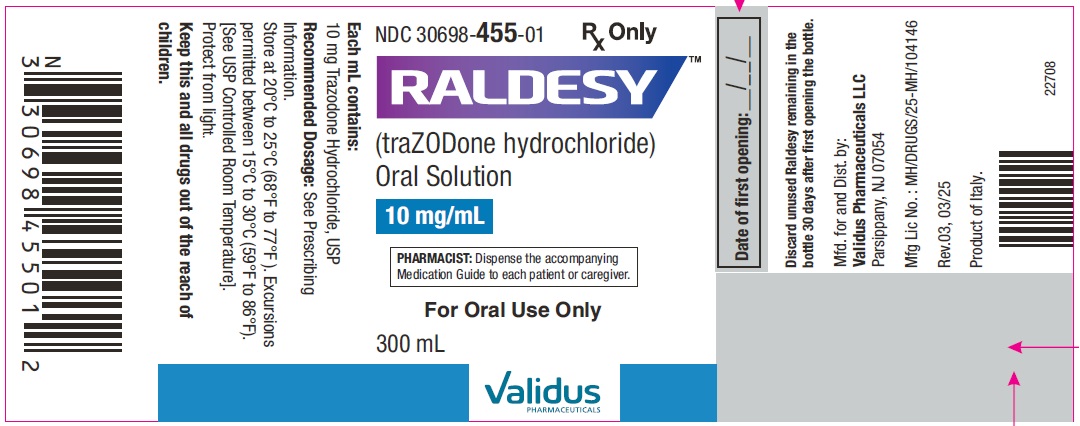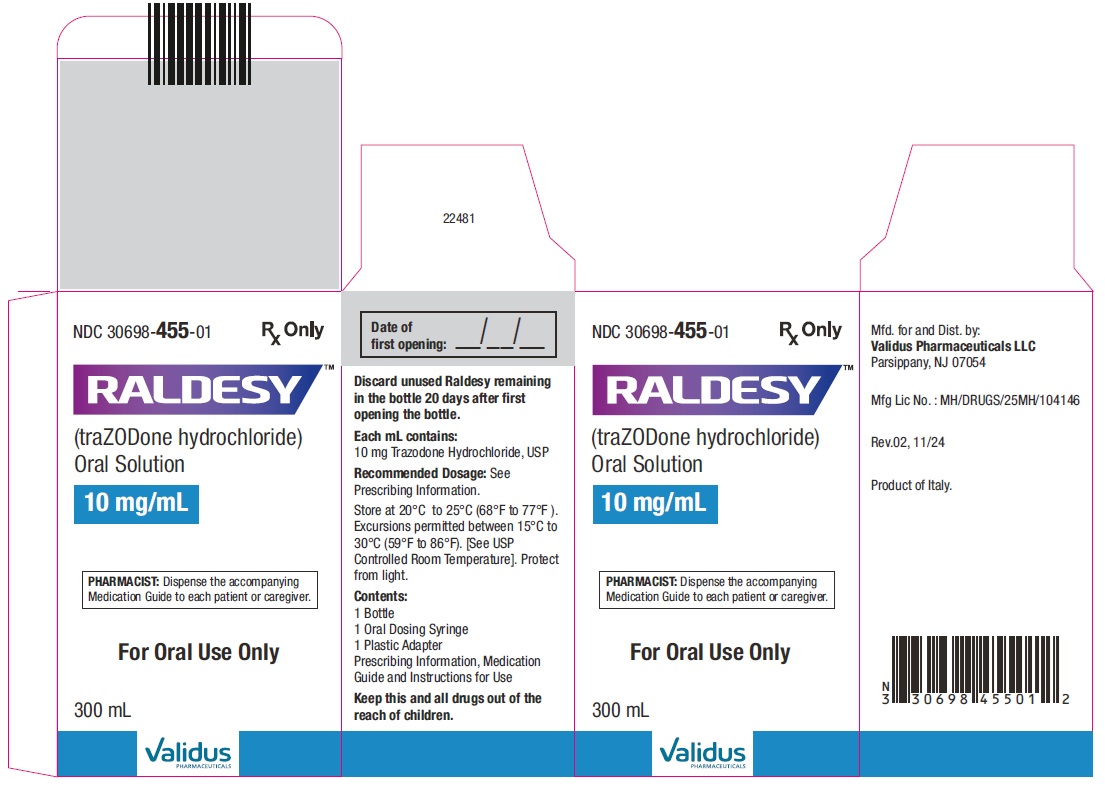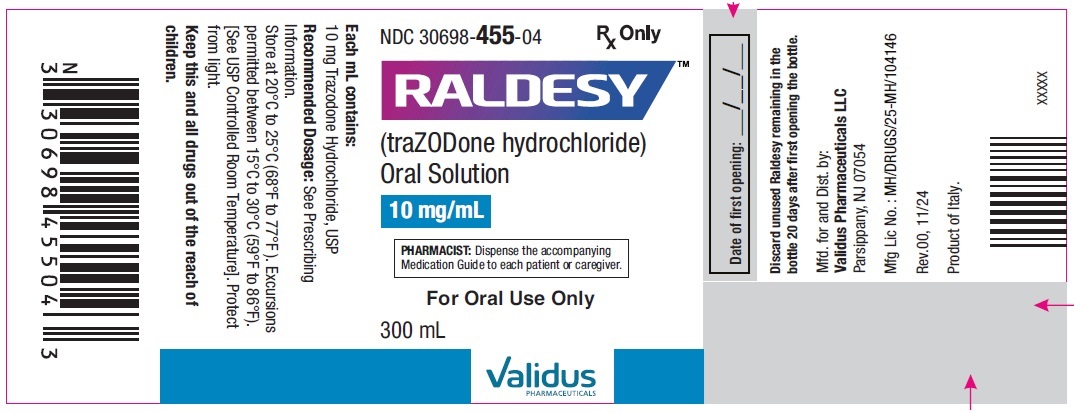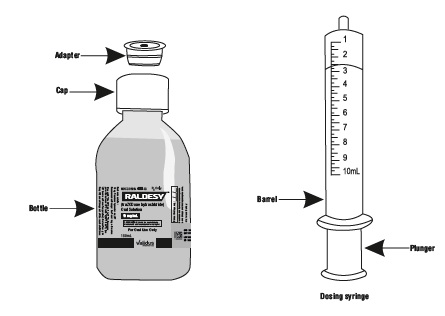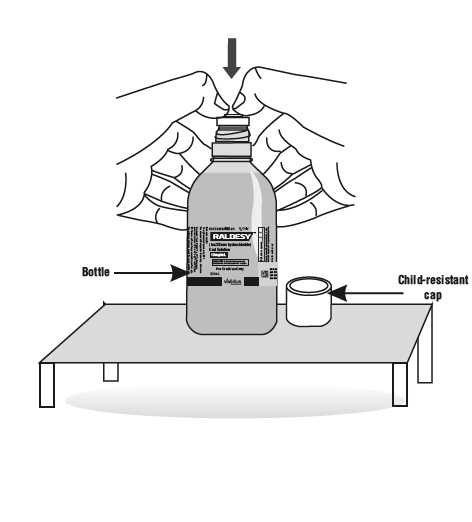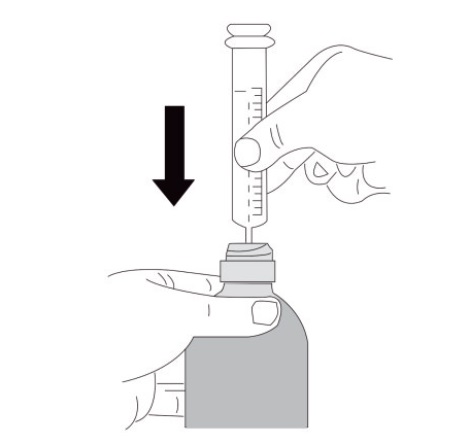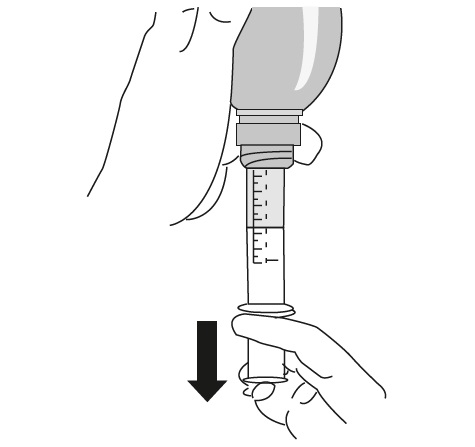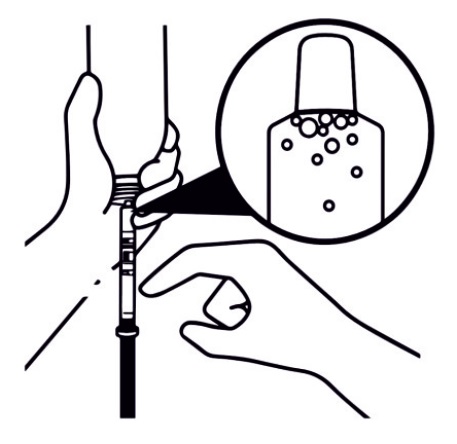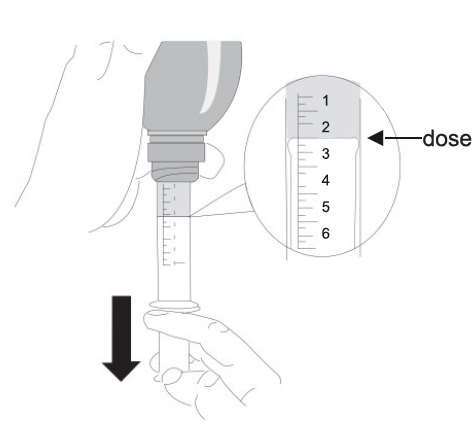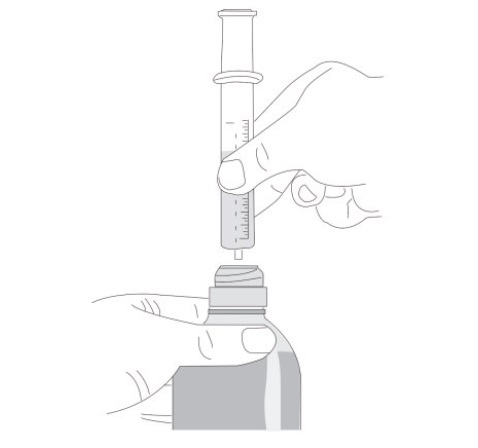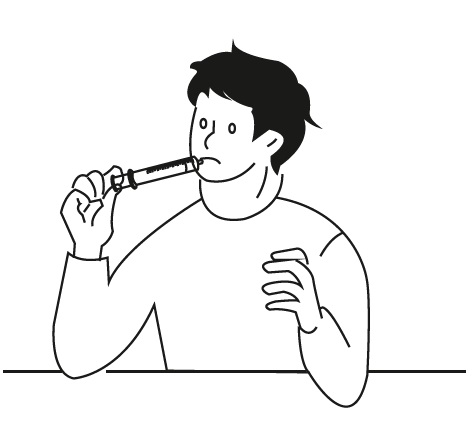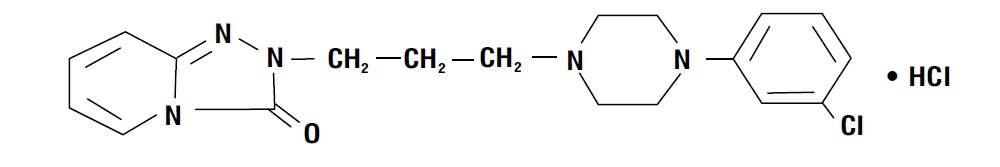 DRUG LABEL: RALDESY

NDC: 30698-455 | Form: SOLUTION
Manufacturer: Validus Pharmaceuticals LLC
Category: prescription | Type: HUMAN PRESCRIPTION DRUG LABEL
Date: 20260123

ACTIVE INGREDIENTS: TRAZODONE HYDROCHLORIDE 10 mg/1 mL
INACTIVE INGREDIENTS: GLYCERIN; PROPYLENE GLYCOL; SORBITOL; SODIUM BENZOATE; SUCRALOSE; PROPYL GALLATE; EDETATE DISODIUM; PHOSPHORIC ACID; WATER

HIGHLIGHTS OF PRESCRIBING INFORMATION

These highlights do not include all the information needed to use RALDESYTMsafely and effectively. See full prescribing information for RALDESYTM.
RALDESYTM(trazodone hydrochloride) oral solution
Initial U.S. Approval: 1981

WARNING: SUICIDAL THOUGHTS and BEHAVIORS

See full prescribing information for complete boxed warning.

- Antidepressants increased the risk of suicidal thoughts and behaviors in pediatric and young adult patients. Closely monitor for clinical worsening and emergence of suicidal thoughts and behaviors (5.1).
- RALDESY is not approved for use in pediatric patients (8.4).

1 INDICATIONS AND USAGE

RALDESY is a selective serotonin reuptake inhibitor (SSRI) indicated for the treatment of major depressive disorder (MDD) in adults (1).

2 DOSAGE AND ADMINISTRATION

- Starting dosage: 150 mg orally in divided doses daily. May be increased by 50 mg per day every three to four days. Maximum dosage: 400 mg per day in divided doses (2.1).
- Administer RALDESY shortly after a meal or light snack (2.1).
- When discontinuing RALDESY, gradually reduce dose (2.5).

3 DOSAGE FORMS AND STRENGTHS

- Oral solution: 10 mg/mL

4 CONTRAINDICATIONS

- Concomitant use of monoamine oxidase inhibitors (MAOIs), or use within 14 days of stopping MAOIs (4).

5 WARNINGS AND PRECAUTIONS

- Serotonin Syndrome: Increased risk when co-administered with other serotonergic agents (e.g., SSRI, SNRI, triptans), but also when taken alone. If it occurs, discontinue RALDESY and initiate supportive treatment (5.2).
- Cardiac Arrhythmias: Increases the QT interval. Avoid use with drugs that also increase the QT interval and in patients with risk factors for prolonged QT interval (5.3).
- Orthostatic Hypotension and Syncope: Warn patients of risk and symptoms of hypotension (5.4).
- Increased Risk of Bleeding: Concomitant use of aspirin, nonsteroidal anti-inflammatory drugs (NSAIDs), other antiplatelet drugs, warfarin, and other anticoagulants may increase this risk (5.5).
- Priapism: Cases of painful and prolonged penile erections and priapism have been reported. Immediate medical attention should be sought if signs and symptoms of prolonged penile erections or priapism are observed (5.6).
- Activation of Mania or Hypomania: Screen for bipolar disorder and monitor for mania or hypomania (5.7).
- Potential for Cognitive and Motor Impairment: Has potential to impair judgment, thinking, and motor skills. Advise patients to use caution when operating machinery (5.9).
- Angle-Closure Glaucoma: Avoid use of antidepressants, including RALDESY, in patients with untreated anatomically narrow angles. (5.10).

6 ADVERSE REACTIONS

Most common adverse reactions (incidence ≥ 5% and twice that of placebo) are: edema, blurred vision, syncope, drowsiness, fatigue, diarrhea, nasal congestion, weight loss (6.1).

To report SUSPECTED ADVERSE REACTIONS, contact Validus Pharmaceuticals LLC at 1-866-982-5438 or FDA at 1-800-FDA-1088 or www.fda.gov/medwatch.

7 DRUG INTERACTIONS

- CNS Depressants: RALDESY may enhance effects of alcohol, barbiturates, or other CNS depressants (7).
- CYP3A4 Inhibitors: Consider RALDESY dose reduction based on tolerability (2.5, 7).
- CYP3A4 Inducers: Increase in RALDESY dosage may be necessary (2.5, 7).
- Digoxin or Phenytoin: Monitor for increased digoxin or phenytoin serum levels (7).
- Warfarin: Monitor for increased or decreased prothrombin time (7).

FULL PRESCRIBING INFORMATION

WARNING: SUICIDAL THOUGHTS and BEHAVIORS

Antidepressants increased the risk of suicidal thoughts and behaviors in pediatric and young adult patients in short-term studies. Closely monitor all antidepressant-treated patients for clinical worsening, and for emergence of suicidal thoughts and behaviors [see Warnings and Precautions (5.1)] . RALDESY is not approved for use in pediatric patients [see Use in Specific Populations (8.4)] .

1 INDICATIONS AND USAGE

RALDESYTMis indicated for the treatment of major depressive disorder (MDD) in adults.

2 DOSAGE AND ADMINISTRATION

2.1 Recommended Dosage

The initial dosage of RALDESY for the treatment of MDD in adults is 150 mg daily, taken orally, in divided doses. The dosage should be initiated at a low-dose and increased gradually, depending on clinical response and an tolerance. Occurrence of drowsiness may require the administration of a major portion of the daily dose at bedtime or a reduction of dosage [see Dosage and Administration (2.5)]

The dose may be increased by 50 mg daily every 3 to 4 days. The maximum recommended dosage for outpatients usually should not exceed 400 mg daily in divided doses. Inpatients (i.e., more severely depressed patients) may be given up to, but not in excess, of 600 mg daily in divided doses.

Administer RALDESY orally after a meal or light snack [see Clinical Pharmacology (12.3)].

2.2 Screen for Bipolar Disorder Prior to Starting RALDESY

Prior to initiating treatment with RALDESY or another antidepressant, screen patients for a personal or family history of bipolar disorder, mania, or hypomania [see Warnings and Precautions (5.7)].

2.3 Switching to or from Monoamine Oxidase Inhibitor Antidepressant

At least 14 days must elapse between discontinuation of a monoamine oxidase inhibitor (MAOI) antidepressant and initiation of RALDESY. In addition, at least 14 days must elapse after stopping RALDESY before starting an MAOI antidepressant [see Contraindications (4), Warnings and Precautions (5.2)].

2.4 Dosage Recommendations for Concomitant Use with Strong CYP3A4 Inhibitors or Inducers

Coadministration with Strong CYP3A4 Inhibitors
Consider reducing RALDESY dose based on tolerability when RALDESY is coadministered with a strong CYP3A4 inhibitor [see Drug Interactions (7.1)].

Coadministration with Strong CYP3A4 Inducers
Consider increasing RALDESY dose based on therapeutic response when RALDESY is coadministered with a strong CYP3A4 inducer [see Drug Interactions (7.1)].

2.5 Discontinuation of Treatment with RALDESY

Adverse reactions may occur upon discontinuation of RALDESY [see Warnings and Precautions (5.8)]. Gradually reduce the dosage rather than stopping RALDESY abruptly whenever possible.

3 DOSAGE FORMS AND STRENGTHS

RALDESY (10 mg/mL) Oral Solution: Clear, colorless solution

4 CONTRAINDICATIONS

RALDESY is contraindicated in patients taking, or within 14 days of stopping, monoamine oxidase inhibitors (MAOIs), including MAOIs such as linezolid or intravenous methylene blue, because of an increased risk of serotonin syndrome [see Warnings and Precautions (5.2), Drug Interactions (7.1)].

5 WARNINGS AND PRECAUTIONS

5.1 Suicidal Thoughts and Behaviors in Pediatric and Young Adult Patients

In pooled analyses of placebo-controlled trials of antidepressant drugs (SSRIs and other antidepressant classes) that included approximately 77,000 adult patients and over 4,500 pediatric patients, the incidence of suicidal thoughts and behaviors in antidepressant-treated patients age 24 years and younger was greater than in placebo-treated patients. There was considerable variation in risk of suicidal thoughts and behaviors among drugs, but there was an increased risk identified in young patients for most drugs studied. There were differences in absolute risk of suicidal thoughts and behaviors across the different indications, with the highest incidence in patients with MDD. The drug-placebo differences in the number of cases of suicidal thoughts and behaviors per 1,000 patients treated are provided in Table 1.

Table 1: Risk Differences of the Number of Cases of Suicidal Thoughts or Behaviors in the Pooled Placebo-Controlled Trials of
Antidepressants in Pediatric and Adult Patients

Age Range (years) | Drug-Placebo Difference in Number of Patients of Suicidal Thoughts or Behaviors per 1,000 Patients Treated
 | Increases Compared to Placebo
<18 | 14 additional patients
18-24 | 5 additional patients
 | Decreases Compared to Placebo
25-64 | 1 fewer patient
≥65 | 6 fewer patients

It is unknown whether the risk of suicidal thoughts and behaviors in pediatric and young adult patients extends to longer-term use, i.e., beyond four months. However, there is substantial evidence from placebo-controlled maintenance trials in adults with MDD that antidepressants delay the recurrence of depression and that depression itself is a risk factor for suicidal thoughts and behaviors.

Monitor all antidepressant-treated patients for clinical worsening and emergence of suicidal thoughts and behaviors, especially during the initial few months of drug therapy and at times of dosage changes. Counsel family members or caregivers of patients to monitor for changes in behavior and to alert the healthcare provider. Consider changing the therapeutic regimen, including possibly discontinuing RALDESY, in patients whose depression is persistently worse, or who are experiencing emergent suicidal thoughts or behaviors.

5.2 Serotonin Syndrome

SSRIs, including RALDESY, can precipitate serotonin syndrome, a potentially life-threatening condition. The risk is increased with concomitant use of other serotonergic drugs (including triptans, tricyclic antidepressants, fentanyl, lithium, tramadol, tryptophan, buspirone, and St. John’s Wort) and with drugs that impair metabolism of serotonin, i.e., MAOIs [see Contraindications (4), Drug Interactions (7.1)]. Serotonin syndrome can also occur when these drugs are used alone.

Serotonin syndrome signs and symptoms may include mental status changes (e.g., agitation, hallucinations, delirium, and coma), autonomic instability (e.g., tachycardia, labile blood pressure, dizziness, diaphoresis, flushing, hyperthermia), neuromuscular symptoms (e.g., tremor, rigidity, myoclonus, hyperreflexia, incoordination), seizures, and gastrointestinal symptoms (e.g., nausea, vomiting, diarrhea).

The concomitant use of RALDESY with MAOIs is contraindicated. In addition, do not initiate RALDESY in a patient being treated with MAOIs such as linezolid or intravenous methylene blue. No reports involved the administration of methylene blue by other routes (such as oral tablets or local tissue injection). If it is necessary to initiate treatment with an MAOI such as linezolid or intravenous methylene blue in a patient taking RALDESY, discontinue RALDESY before initiating treatment with the MAOI [see Contraindications (4), Drug Interactions (7.1)].

Monitor all patients taking RALDESY for the emergence of serotonin syndrome. Discontinue treatment with RALDESY and any concomitant serotonergic agents immediately if the above symptoms occur, and initiate supportive symptomatic treatment. If concomitant use of RALDESY with other serotonergic drugs is clinically warranted, inform patients of the increased risk for serotonin syndrome and monitor for symptoms.

5.3 Cardiac Arrhythmias

Clinical studies indicate that trazodone hydrochloride may be arrhythmogenic in patients with preexisting cardiac disease. Arrhythmias identified include isolated PVCs, ventricular couplets, tachycardia with syncope, and torsade de pointes. Postmarketing reports, including torsade de pointes have been reported at doses of 100 mg or less with the immediate-release trazodone hydrochloride tablets. RALDESY should also be avoided in patients with a history of cardiac arrhythmias, as well as other circumstances that may increase the risk of the occurrence of torsade de pointes and/or sudden death, including symptomatic bradycardia, hypokalemia or hypomagnesemia, and the presence of congenital prolongation of the QT interval. RALDESY is not recommended for use during the initial recovery phase of myocardial infarction. Caution should be used when administering RALDESY to patients with cardiac disease and such patients should be closely monitored, since antidepressant drugs (including RALDESY) may cause cardiac arrhythmias [see Adverse Reactions (6.2)] .

Trazodone hydrochloride prolongs the QT/QTcinterval. The use of RALDESY Should be avoided in patients with known QT prolongation or in combination with other drugs that are inhibitors of CYP3A4 (e.g., itraconazole, clarithromycin, voriconazole), or known to prolong QT interval including Class 1A antiarrhythmics (e.g., quinidine, procainamide) or Class 3 antiarrhythmics (e.g., amiodarone, sotalol), certain antipsychotic medications (e.g., ziprasidone, chlorpromazine, thioridazine), and certain antibiotics (e.g., gatifloxacin). Concomitant administration of drugs may increase the risk of cardiac arrhythmia [see Drug Interactions (7.1)].

5.4 Orthostatic Hypotension and Syncope

Hypotension, including orthostatic hypotension and syncope has been reported in patients receiving trazodone hydrochloride. Concomitant use with an antihypertensive may require a reduction in the dose of the antihypertensive drug.

5.5 Increased Risk of Bleeding

Drugs that interfere with serotonin reuptake inhibition, including RALDESY, increase the risk of bleeding events. Concomitant use of aspirin, nonsteroidal anti-inflammatory drugs (NSAIDS), other antiplatelet drugs, warfarin, and other anticoagulants may add to this risk. Case reports and epidemiological studies (case-control and cohort design) have demonstrated an association between use of drugs that interfere with serotonin reuptake and the occurrence of gastrointestinal bleeding. Bleeding events related to drugs that interfere with serotonin reuptake have ranged from ecchymosis, hematoma, epistaxis, and petechiae to life-threatening hemorrhages.

Inform patients about the risk of bleeding associated with the concomitant use of RALDESY and antiplatelet agents or anticoagulants. For patients taking warfarin, carefully monitor coagulation indices when initiating, titrating, or discontinuing RALDESY.

5.6 Priapism

Cases of priapism (painful erections greater than 6 hours in duration) have been reported in males receiving trazodone hydrochloride tablets. Priapism, if not treated promptly, can result in irreversible damage to the erectile tissue. Males who have an erection lasting greater than 4 hours, whether painful or not, should immediately discontinue the drug and seek emergency medical attention [see Adverse Reactions (6.2), Overdosage (10)].

RALDESY should be used with caution in males who have conditions that might predispose them to priapism (e.g., sickle cell anemia, multiple myeloma, or leukemia), or in men with anatomical deformation of the penis (e.g., angulation, cavernosal fibrosis, or Peyronie’s disease).

5.7 Activation of Mania or Hypomania

In patients with bipolar disorder, treating a depressive episode with RALDESY or another antidepressant may precipitate a mixed/manic episode. Activation of mania/hypomania has been reported in a small proportion of patients with major affective disorder who were treated with antidepressants. Prior to initiating treatment with RALDESY, screen patients for any personal or family history of bipolar disorder, mania, or hypomania [see Dosage and Administration (2.3)] .

5.8 Discontinuation Syndrome

Adverse reactions after discontinuation of serotonergic antidepressants, particularly after abrupt discontinuation, include: nausea, sweating, dysphoric mood, irritability, agitation, dizziness, sensory disturbances (e.g., paresthesia, such as electric shock sensations), tremor, anxiety, confusion, headache, lethargy, emotional lability, insomnia, hypomania, tinnitus, and seizures. A gradual reduction in dosage rather than abrupt cessation is recommended whenever possible [See Dosage and Administration (2.6)].

5.9 Potential for Cognitive and Motor Impairment

RALDESYTM may cause somnolence or sedation and may impair the mental and/or physical ability required for the performance of potentially hazardous tasks. Patients should be cautioned about operating hazardous machinery, including automobiles, until they are reasonably certain that the drug treatment does not affect them adversely.

5.10 Angle-Closure Glaucoma

The pupillary dilation that occurs following use of many antidepressant drugs including RALDESY may trigger an angle closure attack in a patient with anatomically narrow angles who does not have a patent iridectomy. Avoid use of antidepressants, including RALDESY, in patients with untreated anatomically narrow angles.

5.11 Hyponatremia

Hyponatremia may occur as a result of treatment with SNRIs and SSRIs, including RALDESY. Cases with serum sodium lower than 110 mmol/L have been reported. Signs and symptoms of hyponatremia include headache, difficulty concentrating, memory impairment, confusion, weakness, and unsteadiness, which can lead to falls. Signs and symptoms associated with more severe and/or acute cases have included hallucination, syncope, seizure, coma, respiratory arrest, and death. In many cases, this hyponatremia appears to be the result of the syndrome of inappropriate antidiuretic hormone secretion (SIADH).

In patients with symptomatic hyponatremia, discontinue RALDESY and institute appropriate medical intervention. Elderly patients, patients taking diuretics, and those who are volume-depleted may be at greater risk of developing hyponatremia with SSRIs and SNRIs [see Use in Specific Populations (8.5)] .

6 ADVERSE REACTIONS

The following serious adverse reactions are described elsewhere in the labeling:

- Suicidal Thoughts and Behaviors in Pediatric and Young Adults Patients [see Boxed Warningand Warnings and Precautions (5.1)]
- Serotonin Syndrome [see Warnings and Precautions (5.2)]
- Cardiac Arrythmias [see Warnings and Precautions (5.3)]
- Orthostatic Hypotension and Syncope [see Warnings and Precautions (5.4)]
- Increased Risk of Bleeding [see Warnings and Precautions (5.5)]
- Priapism [see Warnings and Precautions (5.6)]
- Activation of Mania or Hypomania [see Warnings and Precautions (5.7)]
- Discontinuation Syndrome [see Warnings and Precautions (5.8)]
- Potential for Cognitive and Motor Impairment [see Warnings and Precautions (5.9)]
- Angle-Closure Glaucoma [see Warnings and Precautions (5.10)]
- Hyponatremia [see Warnings and Precautions (5.11)]

6.1 Clinical Trials Experience

Because clinical trials are conducted under widely varying conditions, adverse reaction rates observed in the clinical trials of a drug cannot be directly compared to rates in the clinical trials of another drug and may not reflect the rates observed in practice.

The safety of RALDESY for the treatment of MDD in adults is based on studies of trazodone hydrochloride tablets. Below is a display of
adverse reactions of trazodone hydrochloride tablets from those studies.

Table 2: Common Adverse Reactions Occurring in ≥ 2% of Trazodone hydrochloride Tablets -treated Patients and Greater than
the Rate of Placebo-Treated Patients as Observed in Controlled Clinical Studies

 | Inpatients |  | Outpatients
 | Trazodone hydrochloride; N=142 | Placebo N=95 | Trazodone hydrochloride; N=157 | Placebo N=158
Allergic
Skin Condition/Edema | 3% | 1% | 7% | 1%
Autonomic
Blurred Vision | 6% | 4% | 15% | 4%
Constipation | 7% | 4% | 8% | 6%
Dry Mouth | 15% | 8% | 34% | 20%
Cardiovascular
Hypertension | 20% | 1% | 1% | *
Hypotension | 7% | 1% | 4% | 0
Syncope | 3% | 2% | 5% | 1%
CNS
Confusion | 5% | 0 | 6% | 8%
Decreased Concentration | 3% | 2% | 1% | 0
Disorientation | 2% | 0 | * | 0
Dizziness/Light-Headedness | 20% | 5% | 28% | 15%
Drowsiness | 24% | 6% | 41% | 20%
Fatigue | 11% | 4% | 6% | 3%
Headache | 10% | 5% | 20% | 16%
Nervousness | 15% | 11% | 6% | 8%
Gastrointestinal
Abdominal/Gastric Disorder | 4% | 4% | 6% | 4%
Diarrhea | 0 | 1% | 5% | 1%
Nausea/Vomiting | 10% | 1% | 13% | 10%
Musculoskeletal
Aches/Pains | 6% | 3% | 5% | 3%
Neurological
Incoordination | 5% | 0 | 2% | *
Tremors | 3% | 1% | 5% | 4%
Other
Eyes Red/Tired/Itching | 3% | 0 | 0 | 0
Head Full-Heavy | 3% | 0 | 0 | 0
Malaise | 3% | 0 | 0 | 0
Nasal/Sinus Congestion | 3% | 0 | 6% | 3%
Weight Gain | 1% | 0 | 5% | 2%
Weight Loss | * | 3% | 6% | 3%

Other adverse reactions occurring at an incidence of <2% with the use of trazodone hydrochloride in the controlled clinical studies: akathisia, allergic reaction, anemia, chest pain, delayed urine flow, early menses, flatulence, hallucinations/delusions, hematuria, hypersalivation, hypomania, impaired memory, impaired speech, impotence, increased appetite, increased libido, increased urinary frequency, missed periods, muscle twitches, numbness, paresthesia, retrograde ejaculation, shortness of breath, and tachycardia/palpitations. Occasional sinus bradycardia has occurred in long-term studies.

6.2 Postmarketing Experience

The following adverse reactions have been identified during post-approval use of trazodone hydrochloride tablets. Because these reactions are reported voluntarily from a population of uncertain size, it is not always possible to estimate their frequency or establish a causal relationship to drug exposure:

Blood and lymphatic system disorders:hemolytic anemia, leukocytosis

Cardiac disorders:cardiospasm, congestive heart failure, conduction block, orthostatic hypotension and syncope, palpitations, bradycardia, atrial fibrillation, myocardial infarction, cardiac arrest, arrhythmia, ventricular ectopic activity, including ventricular tachycardia and QT prolongation. Prolonged QT interval, torsade de pointes, and ventricular tachycardia have been reported at doses of 100 mg per day or less [see Warnings and Precautions (5.3)].

Endocrine disorders:inappropriate ADH syndrome

Eye disorders:diplopia

Gastrointestinal disorders:increased salivation, nausea/vomiting

General disorders and administration site conditions:chills, edema, unexplained death, weakness

Hepatobiliary disorders:cholestasis, jaundice, hyperbilirubinemia, liver enzyme alterations

Investigations:increased amylase

Metabolism and nutrition disorders:methemoglobinemia

Nervous system disorders:aphasia, ataxia, cerebrovascular accident, extrapyramidal symptoms, grand mal seizures, paresthesia, tardive dyskinesia, vertigo

Psychiatric disorders:abnormal dreams, agitation, anxiety, hallucinations, insomnia, paranoid reaction, psychosis, stupor

Renal and urinary disorders:urinary incontinence, urinary retention

Reproductive system and breast disorders:breast enlargement or engorgement, clitorism, lactation, priapism [see Warnings and Precautions (5.6)]

Respiratory, thoracic and mediastinal disorders:apnea

Skin and subcutaneous tissue disorders:alopecia, hirsutism, leukonychia, pruritus, psoriasis, rash, urticaria

Vascular disorders:vasodilation

7 DRUG INTERACTIONS

Table 3 displays clinically significant drug Interactions with RALDESY.

Table 3: Clinically Significant Drug Interactions with RALDESY

Monoamine Oxidase Inhibitors (MAOIs)
Clinical Impact: | The concomitant use of MAOIs and serotonergic drugs including RALDESY increases the risk of serotonin syndrome.
Intervention: | RALDESY is contraindicated in patients taking MAOIs, including MAOIs such as linezolid or intravenous methylene blue [see Contraindications (4), Dosage and Administration (2.3, 2.4), and Warnings and Precautions (5.2)].
Other Serotonergic Drugs
Clinical Impact: | The concomitant use of serotonergic drugs, including RALDESY and other serotonergic drugs increases the risk of serotonin syndrome.
Intervention: | Monitor patients for signs and symptoms of serotonin syndrome, particularly during RALDESY initiation. If serotonin syndrome occurs, consider discontinuation of RALDESY and/or concomitant serotonergic drugs [see Warnings and Precautions (5.2)].
Antiplatelet Agents and Anticoagulants
Clinical Impact: | Serotonin release by platelets plays an important role in hemostasis. The concurrent use of an antiplatelet agent or anticoagulant with RALDESY may potentiate the risk of bleeding.
Intervention: | Inform patients of the increased risk of bleeding with the concomitant use of RALDESY and antiplatelet agents and anticoagulants. For patients taking warfarin, carefully monitor the international normalized ratio (INR) when initiating or discontinuing RALDESY [see Warnings and Precautions (5.5)].
Strong CYP3A4 Inhibitors
Clinical Impact: | The concomitant use of RALDESY and strong CYP3A4 inhibitors increased the exposure of trazodone compared to the use of RALDESY alone.
Intervention: | If RALDESY is used with a potent CYP3A4 inhibitor, the risk of adverse reactions, including cardiac arrhythmias, may be increased and a lower dose of RALDESY should be considered [see Dosage and Administration (2.5), Warnings and Precautions (5.3)].
Strong CYP3A4 Inducers
Clinical Impact: | The concomitant use of RALDESY and strong CYP3A4 inducers decreased the exposure of trazodone compared to the use of RALDESY alone.
Intervention: | Patients should be closely monitored to see if there is a need for an increased dose of RALDESY when taking CYP3A4 inducers [see Dosage and Administration (2.5)].
Digoxin and Phenytoin
Clinical Impact: | Digoxin and phenytoin are narrow therapeutic index drugs. Concomitant use of RALDESY can increase digoxin or phenytoin concentrations.
Intervention: | Measure serum digoxin or phenytoin concentrations before initiating concomitant use of RALDESY. Continue monitoring and reduce digoxin or phenytoin dose as necessary.
Central Nervous System (CNS) Depressants
Clinical Impact: | RALDESY may enhance the response CNS depressants.
Intervention: | Patients should be counseled that RALDESY may enhance the response to alcohol, barbiturates, and other CNS depressants.
QT Interval Prolongation
Clinical Impact: | Concomitant use of drugs that prolong the QT interval may add to the QT effects of RALDESY and increase the risk of cardiac arrhythmia.
Intervention: | Avoid the use of RALDESY in combination with other drugs known to prolong QTc [see Warnings and Precautions (5.3)] .

8 USE IN SPECIFIC POPULATIONS

8.1 Pregnancy

Pregnancy Exposure Registry
There is a pregnancy exposure registry that monitors pregnancy outcomes in women exposed to antidepressants during pregnancy. Healthcare providers should encourage patients to enroll by calling the National Pregnancy Registry for Antidepressants at 1-866-961-2388 or visiting online at https://womensmentalhealth.org/research/pregnancyregistry/antidepressants/.

Risk Summary
Published prospective cohort studies, case series, and case reports over several decades with trazodone hydrochloride tablets use in pregnant women have not identified any drug-associated risks of major birth defects, miscarriage, or other adverse maternal or fetal outcomes (see Data). There are risks associated with untreated depression in pregnancy (see Clinical Considerations) . Trazodone hydrochloride has been shown to cause increased fetal resorption and other adverse effects on the fetus in the rat when given at dose levels approximately 7.3 to 11 times the maximum recommended human dose (MRHD) of 400 mg/day in adults on a mg/m^2basis. There was also an increase in congenital anomalies in the rabbit at approximately 7.3 to 22 times the MRHD on a mg/m^2basis (see Data).

The background risk of major birth defects and miscarriage for the indicated population is unknown. All pregnancies have a background risk of birth defect, loss, or other adverse outcomes. In the U.S. general population, the estimated background risk of major birth defects and miscarriage in clinically recognized pregnancies is 2% to 4% and 15% to 20%, respectively.

Clinical Considerations
Disease-associated maternal and/or embryofetal risk
Women who discontinue antidepressants during pregnancy are more likely to experience a relapse of major depression than women who continue antidepressants. This finding is from a prospective, longitudinal study of 201 pregnant women with a history of major depressive disorder who were euthymic and taking antidepressants at the beginning of pregnancy. Consider the risk of untreated depression when discontinuing or changing treatment with antidepressant medication during pregnancy and postpartum.

Data
Human Data
While available studies cannot definitively establish the absence of risk, published data from prospective cohort studies, case series, and case reports over several decades have not identified an association with trazodone use during pregnancy and major birth defects, miscarriage, or other adverse maternal or fetal outcomes. All available studies have methodological limitations, including small sample size and inconsistent comparator groups.

Animal Data
No teratogenic effects were observed when trazodone was given to pregnant rats and rabbits during the period of organogenesis at oral doses up to 450 mg/kg/day. This dose is 11 and 22 times, in rats and rabbits, respectively, the maximum recommended human dose (MRHD) of 400 mg/day in adults on a mg/m^2basis. Increased fetal resorption and other adverse effects on the fetus in rats at 7.3 to 11 times the MRHD and increase in congenital anomalies in rabbits at 7.3 to 22 times the MRHD on a mg/m^2basis were observed. No further details on these studies are available.

8.2 Lactation

Risk Summary
Data from published literature report the transfer of trazodone into human milk. There are no data on the effect of trazodone on milk production. Limited data from postmarketing reports have not identified an association of adverse effects on the breastfed child.
The developmental and health benefits of breastfeeding should be considered along with the mother’s clinical need for RALDESY and any potential adverse effects on the breastfed child from RALDESY or from the underlying maternal condition.

8.4 Pediatric Use

Safety and effectiveness of RALDESY in the pediatric patients have not been established.

Antidepressants increased the risk of suicidal thoughts and behaviors in pediatric patients [see Boxed Warning, Warnings and Precautions (5.1)].

8.5 Geriatric Use

Reported clinical literature and experience with trazodone has not identified differences in responses between geriatric and younger patients. However, as experience with trazodone hydrochloride in geriatric patients is limited, RALDESY should be used with caution in these patients.

Serotonergic antidepressants have been associated with cases of clinically significant hyponatremia in elderly patients, who may be at greater risk for this adverse reaction [see Warnings and Precautions (5.11)].

8.6 Renal Impairment

Trazodone has not been studied in patients with renal impairment. RALDESY should be used with caution in this population.

8.7 Hepatic Impairment

Trazodone has not been studied in patients with hepatic impairment. RALDESY should be used with caution in this population.

9 DRUG ABUSE AND DEPENDENCE

9.1 Controlled Substance

Trazodone hydrochloride is not a controlled substance.

9.2 Abuse

Although trazodone hydrochloride has not been systematically studied in preclinical or clinical studies for its potential for abuse, no indication of drug-seeking behavior was seen in the clinical studies with trazodone hydrochloride.

10 OVERDOSAGE

Death from overdose has occurred in patients ingesting trazodone and other CNS depressant drugs concurrently (alcohol; alcohol and chloral hydrate and diazepam; amobarbital; chlordiazepoxide; or meprobamate).

The most severe reactions reported to have occurred with overdose of trazodone alone have been priapism, respiratory arrest, seizures, and ECG changes, including QT prolongation. The reactions reported most frequently have been drowsiness and vomiting. Overdosage may cause an increase in incidence or severity of any of the reported adverse reactions.

There is no specific antidote for trazodone hydrochloride overdose. Consider contacting the Poison Help line 1-888-222-1222 or a medical toxicologist for additional overdose management recommendations.

11 DESCRIPTION

RALDESY contains trazodone hydrochloride, a selective serotonin reuptake inhibitor and 5HT2 receptor antagonist. Trazodone hydrochloride is a triazolopyridine derivative designated as 2-[3-[4-(3-chlorophenyl)-1- piperazinyl]propyl]-1,2,4-triazolo [4,3-a]pyridin-3(2 H)-one hydrochloride. It is a white odorless crystalline powder which is freely soluble in water. The structural formula is represented as follows:

Molecular Formula: C19H22CIN5O • HCL

Molecular Weight:408.33

RALDESY Oral Solution: Each mL contains 10 mg of Trazodone Hydrochloride, USP equivalent to 9.1 mg of trazodone base. The following inactive ingredients: disodium edetate, glycerin, ortho phosphoric acid, propyl gallate, propylene glycol, purified water, sodium benzoate,sorbitol, and sucralose. The pH of the oral solution is 3.8 to 4.8.

12 CLINICAL PHARMACOLOGY

12.1 Mechanism of Action

The mechanism of trazodone’s antidepressant action is unclear, but is thought to be related to its enhancement of serotonergic activity in the CNS. Trazodone is both a selective serotonin reuptake inhibitor (SSRI) and a 5HT2 receptor antagonist and the net result of this action on serotonergic transmission and its role in trazodone’s antidepressant effect is unknown.

12.2 Pharmacodynamics

Preclinical studies have shown that trazodone selectively inhibits neuronal reuptake of serotonin (Ki = 367 nM) and acts as an antagonist at 5-HT-2A (Ki = 35.6 nM) serotonin receptors. Trazodone is also an antagonist at several other monoaminergic receptors including 5-HT2B (Ki = 78.4 nM), 5-HT2C (Ki = 224 nM), α1A (Ki = 153 nM), α2C (Ki = 155 nM) receptors and it is a partial agonist at 5- HT1A (Ki = 118 nM) receptor.

Trazodone antagonizes alpha 1-adrenergic receptors, a property which may be associated with postural hypotension.

12.3 Pharmacokinetics

No clinically significant difference in pharmacokinetics of trazodone was observed between RALDESY and immediate-release trazodone hydrochloride tablet administered under fed conditions.

Absorption
Peak plasma levels occur approximately one hour after administration under fed conditions.

Effect of Food
Ingestion of a high-fat meal with RALDESY lowers mean Cmaxof trazodone by 31% and increases mean AUC by 8%. Median Tmaxwas similar between fed and fasted conditions.

Distribution
Trazodone is 89% to 95% protein bound in vitroat concentrations attained with therapeutic doses in humans.

Metabolism
In vitro studies in human liver microsomes show that trazodone is metabolized, via oxidative cleavage, to an active metabolite, m-chlorophenylpiperazine (mCPP) by CYP3A4. Other metabolic pathways that may be involved in the metabolism of trazodone have not been well characterized. Trazodone is extensively metabolized; less than 1% of an oral dose is excreted unchanged in the urine.

Elimination
The average terminal elimination half-life of RALDESY under fed state is 18 hours.

13 NONCLINICAL TOXICOLOGY

13.1 Carcinogenesis, Mutagenesis, Impairment of Fertility

Carcinogenesis
No drug- or dose-related occurrence of carcinogenesis was evident in rats receiving trazodone in daily oral doses up to 7.3 times the maximum recommended human dose (MRHD) of 400 mg/day in adults on a mg/m^2basis.

Mutagenesis
No genotoxicity studies were conducted with trazodone.

Impairment of Fertility
Trazodone has no effect on fertility in rats at doses up to 7.3 times the MRHD in adults on a mg/m^2basis.

14 CLINICAL STUDIES

The efficacy of RALDESY for the treatment of MDD in adults is based on studies of trazodone hydrochloride tablets.

16 HOW SUPPLIED/STORAGE AND HANDLING

How Supplied
RALDESYTMcontains 10 mg/mL of trazodone hydrochloride. It is a clear, colorless solution and is supplied as:

150 mL amber glass bottle

- NDC 30698-455-03 with child-resistant cap along with a 10 mL calibrated oral dosing syringe and bottle adapter.

150 mL white, opaque, high-density polyethylene (HDPE) bottle

- NDC 30698-455-02 with child-resistant cap along with a 10 mL calibrated oral dosing syringe and bottle adapter.

300 mL amber glass bottle

- NDC 30698-455-04 with child-resistant cap along with a 10 mL calibrated oral dosing syringe and bottle adapter.

300 mL white, opaque, HDPE bottle

- NDC 30698-455-01 with child-resistant cap along with a 10 mL calibrated oral dosing syringe and bottle adapter.

The bottle, bottle adapter and the dosing syringe are placed in a carton.

Storage and Handling
Store at 20°C to 25°C (68°F to 77°F). Excursions permitted between 15°C to 30°C (59°F to 86°F) [see USP Controlled Room Temperature].
Protect from light. Discard any unused RALDESY remaining in the bottle 20 days after first opening the bottle.

17 PATIENT COUNSELING INFORMATION

Advise the patient to read the FDA-approved patient labeling (Medication Guide and Instructions for Use).

Suicidal Thoughts and Behaviors
Advise patients and caregivers to look for the emergence of suicidality, especially early during treatment and when the dosage is adjusted up or down and instruct them to report such symptoms to the healthcare provider [ see Box Warningand Warnings and Precautions (5.1)].

Dosage and Administration
Advise patients that RALDESY should be taken shortly after a meal or light snack. Advise patients regarding the importance of following dosage titration instructions [see Dosage and Administration (2)] .

Serotonin Syndrome
Caution patients about the risk of serotonin syndrome, particularly with the concomitant use of RALDESY with other serotonergic drugs including triptans, tricyclic antidepressants, fentanyl, lithium, tramadol, tryptophan, buspirone, St. John’s Wort, and with drugs that impair metabolism of serotonin (in particular, MAOIs, both those intended to treat psychiatric disorders and also others, such as linezolid). Patients should contact their health care provider or report to the emergency room if they experience signs or symptoms of serotonin syndrome [see Warnings and Precautions (5.2)and Drug Interactions (7)] .

Increased Risk of Bleeding
Inform patients about the concomitant use of RALDESY with aspirin, NSAIDs, other antiplatelet drugs, warfarin, or other anticoagulants because the combined use of drugs that interfere with serotonin reuptake and these medications has been associated with an increased risk of bleeding. Advise them to inform their health care providers if they are taking or planning to take any prescription or over-the-counter medications that increase the risk of bleeding [see Warnings and Precautions (5.5)] .

Activation of Mania or Hypomania
Advise patients and their caregivers to observe for signs of activation of mania/hypomania and instruct them to report such symptoms to the healthcare provider [see Warnings and Precautions (5.7)].

Discontinuation Syndrome
Advise patients not to abruptly discontinue RALDESY and to discuss any tapering regimen with their healthcare provider. Adverse reactions can occur when RALDESY is discontinued [see Warnings and Precautions (5.8)].

Concomitant Medications
Advise patients to inform their health care providers if they are taking, or plan to take any prescription or over-the-counter medications since there is a potential for interactions [see Drug Interactions (7.1)].

Pregnancy
Advise patients to notify their healthcare provider if they become pregnant or intend to become pregnant during therapy with RALDESY. Advise patients that there is a pregnancy exposure registry that monitors pregnancy outcomes in women exposed to RALDESY during pregnancy [see Use in Special Populations (8.1)].

Manufactured for and distributed by:
Validus Pharmaceuticals LLC
Parsippany, NJ 07054

MEDICATION GUIDE

RALDESYTM(ral DEH see)

(trazodone hydrochloride)

oral solution

What is the most important information I should know about RALDESY?

RALDESY can cause serious side effects, including:

• Increased risk of suicidal thoughts or actions.RALDESY and other antidepressant medicines increase the risk of suicidal thoughts and actions in people 24 years of age and younger, especially within the first few months of treatment or when the dose is changed. RALDESY is not for use in children.

◦ Depression and other mental illnesses are the most important causes of suicidal thoughts and actions.

How can I watch for and try to prevent suicidal thoughts and actions?

◦ Pay close attention to any changes, especially sudden changes in mood, behaviors, thoughts, or feelings if you develop suicidal thoughts or actions. This is very important when an antidepressant medicine is started or when the dose is changed.

◦ Call your healthcare provider right away to report new or sudden changes in mood, behavior, thoughts or feelings, or if you develop suicidal thoughts or actions.

◦ Keep all follow-up visits with your healthcare provider as scheduled. Call your healthcare provider between visits as needed, especially if you are worried about symptoms.

Call a healthcare provider right away if you have any of the following symptoms, especially if they are new, worse, or worry you:

• attempts to commit suicide • acting on dangerous impulses • acting aggressive or violent

• thoughts about suicide or dying • new or worse depression • a new or worse anxiety or panic attacks

• feeling agitated, restless, angry, or irritable • trouble sleeping • an increase in activity or talking more than what is normal for you

• other unusual changes in behavior and mood

See “What are the possible side effects of RALDESY?”for more information about side effects.

What is RALDESY?

RALDESY is a prescription medicine used in adults to treat major depressive disorder (MDD).

It is not known if RALDESY is safe and effective for use in children.

Who should not take RALDESY?

Do not take RALDESY if you:

• are taking, or have stopped taking within the last 14 days, a medicine called Monoamine Oxidase Inhibitor (MAOI), including the antibiotic linezolid and intravenous methylene blue

Ask your healthcare provider or pharmacist is you are not sure if you take an MAOI, including the antibiotic linezolid or intravenous blue.

Do not start taking an MAOI for at least 14 days after you stop treatment with RALDESY.

Before taking RALDESY tell your healthcare provider about all of your medical conditions, including if you:

• have or have a family history of heart problems, including fast or slow heartbeat, or changes in the electrical activity of your heart (QT prolongation)

• have ever had a heart attack

• have or have had bleeding problems

• are male and have conditions that may cause a prolonged or painful erection (priapism) such as sickle cell anemia, multiple myeloma, leukemia, or a deformed penis

• have or have a family history of bipolar disorder, mania, or hypomania

• have high pressure in the eye (glaucoma)

• have low sodium levels in your blood

• are pregnant or plan to become pregnant. It is not known if RALDESY will harm your unborn baby. Talk to your healthcare provider about the risks to you or your unborn baby if you take RALDESY during pregnancy.

◦ Tell your healthcare provider right away if you become pregnant or think you are pregnant during treatment with RALDESY.

◦ There is a pregnancy registry for females who are exposed to RALDESY during pregnancy. The purpose of this registry is to collect information about the health of females exposed to RALDESY and their baby.
If you become pregnant during treatment with RALDESY, talk to your healthcare provider about registering with the National Pregnancy Registry for Antidepressants. You can register by calling 1-866-961-2388 or visiting online at https://womensmentalhealth.org/research/pregnancyregistry/antidepressants/.

• are breastfeeding or plan to breastfeed. RALDESY passes into your breast milk. Talk to your healthcare provider about the best way to feed your baby during treatment with RALDESY.

Tell your healthcare provider about all the medicines you take, including prescription and over-the-counter medicines, vitamins, and herbal supplements.

RALDESY and some other medicines may affect each other causing serious side effects. RALDESY may affect the way other medicines work and other medicines may affect the way RALDESY works.

Especially tell your healthcare provider if you take:

• MAOIs

• medicines used to treat migraine headache called triptans

• medicines used to treat mood, anxiety, psychotic or thought disorders, including tricyclic antidepressants, lithium, selective serotonin reuptake inhibitors (SSRIs), serotonin and norepinephrine reuptake inhibitors (SNRIs), buspirone, or antipsychotics

• tramadol, fentanyl, or other opioids

• over-the-counter supplements such as tryptophan or St. John’s Wort

• medicines used to treat high blood pressure

• medicines used to treat irregular heartbeats

• medicines that affect blood clotting such as aspirin, nonsteroidal anti-inflammatory drugs (NSAIDS), warfarin or other blood thinners

• digoxin

• medicines used to treat seizures or convulsions

• diuretics

Ask your healthcare provider if you are not sure if you are taking any of these medicines. Your healthcare provider can tell you if it is safe to take RALDESY with your other medicines.

Do notstart or stop any other medicines during treatment with RALDESY without talking to your healthcare provider first. Stopping RALDESY suddenly may cause you to have serious side effects. See, “What are the possible side effects of RALDESY?”

Know the medicines you take. Keep a list of them to show it to your healthcare provider and pharmacist when you get a new medicine.

How should I take RALDESY?

See the detailed Instructions for Use that comes with RALDESY for information on how to take RADELSY oral solution.

• Take RALDESY exactly as your healthcare provider tells you. Your healthcare provider may need to change your dose of RALDESY until it is the right dose for you.

• If you feel sleepy after taking RALDESY, talk to your healthcare provider. Your healthcare provider may change your dose or the time of day you take your RALDESY.

• Take RALDESY after a meal or light snack.

• Do not stop taking RALDESY without talking to your healthcare provider.

• If you take too much RALDESY, call your healthcare provider, your Poison Help Line at 1-800-222-1222, or go to the nearest hospital emergency room right away.

What should I avoid while taking RALDESY?

• Do notdrive, operate heavy machinery, or do other dangerous activities until you know how RALDESY affects you. RALDESY can cause sleepiness or may affect your ability to make decisions, think clearly, or react quickly.

• Do notdrink alcohol or take other medicines that make you sleepy or dizzy during treatment with RALDESY until you talk with your healthcare provider. RALDESY may make your sleepiness or dizziness worse if you drink alcohol or take other medicines that cause sleepiness or dizziness.

What are the possible side effects of RALDESY?

RALDESY can cause serious side effects, including:

• See “What is the most important information I should know about RALDESY?”

Serotonin syndrome. A potentially life-threating problem called serotonin syndrome can happen when you take RALDESY with certain other medicines. See “Who should not take RALDESY?” Call your healthcare provider or go to the nearest hospital emergency room right awayif you have any of the following signs and symptoms of serotonin syndrome:

◦ agitation ◦ flushing

◦ seeing or hearing things that are not real (hallucinations) ◦ high body temperature (hyperthermia)

◦ confusion ◦ shaking (tremors), stiff muscles, or muscle twitching

◦ coma ◦ loss of coordination

◦ fast heartbeat ◦ seizures

◦ changes in blood pressure ◦ nausea, vomiting, diarrhea

◦ sweating ◦ dizziness

• Changes in the electrical activity of your heart (QT prolongation).Call your healthcare provider right away if you have any of the following symptoms: abnormal heartbeats, dizziness, feel lightheaded or faint.

• Low blood pressure and fainting.Low blood pressure can happen when you change positions from sitting to standing or laying down. You may feel dizzy, lightheaded, or faint.

• Increased risk of bleeding.Taking RALDESY with aspirin, non-steroidal anti-inflammatory drugs (NSAIDs), warfarin, or blood thinners may add to this risk. Tell your healthcare provider right away about any unusual bleeding or bruising.

• Painful erection lasting for more than 6 hours (priapism).If you have an erection that lasts more than 4 hours, get medical help right away.

• Manic episodes.Manic episodes may happen in people with bipolar disorder who take RALDESY. Symptoms may include:

◦ greatly increased energy ◦ severe problems sleeping

◦ racing thoughts ◦ reckless behavior

◦ unusually grand ideas ◦ excessive happiness or irritability

◦ talking more or faster than usual

• Discontinuation syndrome.Suddenly stopping RALDESY may cause you to have serious side effects. Your healthcare provider may want to decrease your dose slowly. Symptoms may include:

◦ nausea ◦ electric shock feeling (paresthesia) ◦ tiredness

◦ sweating ◦ tremor ◦ problems sleeping

◦ changes in your mood ◦ anxiety ◦ hypomania

◦ irritability and agitation ◦ confusion ◦ ringing in the ears (tinnitus)

◦ dizziness ◦ headache ◦ seizures

• Eye problems (angle-closure glaucoma).RALDESY can cause a type of eye problem called angle-closure glaucoma in people with certain eye conditions. You may want to undergo an eye examination to see if you are at risk and receive preventative treatment if you are. Call your healthcare provider if you have changes in your vision, eye pain, or swelling or redness in or around the eye.

• Low sodium in your blood (hyponatremia).Low sodium levels in your blood that may be serious and may cause death, can happen during treatment with RALDESY. Elderly people and people who take certain medicines may be at greater risk for this. Signs and symptoms may include:

◦ headache ◦ confusion

◦ difficulty concentrating ◦ weakness and unsteadiness on your feet, which can lead to falls

◦ memory changes

◦ talking more or faster than usual

In more severe or sudden cases, signs and symptoms include:

◦ seeing or hearing things that are not real ◦ coma

(hallucinations) ◦ stopping breathing (respiratory arrest) to falls

◦ fainting

◦ seizures

The most common side effects of RALDESY include:

• swelling • tiredness

• blurred vision • diarrhea

• fainting • stuffy nose

• sleepiness • weight loss

These are not all of the possible side effects of RALDESY.

Call your doctor for medical advice about side effects. You may report side effects to FDA at 1-800 FDA-1088.

How should I store RALDESY?

• Store RALDESY at room temperature between 68°F to 77°F (20°C to 25°C).

• RALDESY comes in a bottle with a child-resistant cap.

• Keep RALDESY out of the light.

• Throw away (discard) RALDESY 20 days after first opening the bottle.

• Safely throw away medicine that is out of date or no longer needed.

Keep RALDESY and all medicines out of the reach of children

General information about the safe and effective use of RALDESY.

Medicines are sometimes prescribed for purposes other than those listed in a Medication Guide. Do not use RALDESY for a condition for which it was not prescribed. Do not give RALDESY to other people, even if they have the same symptoms that you have. It may harm them. You can ask your pharmacist or healthcare provider for information about RALDESY that is written for health professional.

What are the ingredients in RALDESY?

Active ingredient:trazodone hydrochloride, USP

Inactive ingredients: disodium edetate, glycerin, ortho phosphoric acid, propyl gallate, propylene glycol, purified water, sodium benzoate, sorbitol, and sucralose.

Manufactured for and distributed by:

Validus Pharmaceuticals LLC

Parsippany, NJ 07054

For more information, go to www.RALDESY.com or call Validus Pharmaceuticals LLC at 1-866-982-5438.

This Medication Guide has been approved by the U.S. Food and Drug Administration Issued: 04/2025

PATIENT COUNSELING INFORMATION

INSTRUCTIONS FOR USE

RALDESYTM(ral DEH see)

(trazodone hydrochloride)

oral solution

This Instructions for Use contains information on how to take RALDESY.

Read this Instructions for Use before you start taking RALDESY for the first time and each time you get a refill. There may be new information. This information does not take the place of talking to your healthcare provider about your medical condition or treatment.

Supplies needed to take RALDESY

Each carton of RALDESY contains:

- 1 bottle of RALDESY oral solution
- 1 plastic adapter
- One 10 mL oral dosing syringe

Important Information You Need to Know Before Taking RALDESY

• For oral use only (taken by mouth).

• Use the plastic adapter and oral dosing syringe that comes in the carton. If you did not receive the plastic adapter and oral dosing syringe, contact your pharmacist.

• Ask your pharmacist how to measure your prescribed doses.

• Take RALDESY exactly as prescribed by your healthcare provider. Do notstop taking RALDESY without first talking to your healthcare provider.

• Take RALDESY after a meal or light snack.

• Check the expiration date on the bottle. If you have not opened the RALDESY bottle, do notuse RALDESY if the expiration date on the bottle has passed. Contact your healthcare provider or pharmacist.

• Do notuse RALDESY 20 days after first opening the bottle.

Preparing the RALDESY bottle

Step 1.Remove the child-resistant cap by pushing it firmly
down and turning it counterclockwise (to the left), as
shown on the top of the child-resistant cap.
Note:Save the child-resistant cap so you can close
the bottle after each use.

Step 2.Hold the open bottle upright on a table and push the
ribbed end of the plastic adapter firmly into the neck of
the bottle as far as you can.

Step 3.Put the child-resistant cap back on the bottle to make
sure the plastic adapter has been fully inserted into
the neck of the bottle.
Note:You may not be able to push the plastic adapter
all the way down, but it will be forced into the bottle
when you put the child-resistant cap back on.
Now the bottle is ready to use with the oral dosing
syringe.
Do notremove the adapter. The plastic adapter must
always stay in the bottle. The child-resistant cap
should seal the bottle in between use.
Write the date of first opening the RALDESY bottle.

Preparing the dose of RALDESY oral solution

Step 4.Push down and turn the child-resistant cap to the left
to open the bottle.
Note:Always replace the cap after use.

Step 5.Check that the plunger is all the way down inside the
barrel of the oral dosing syringe.

Step 6.Keep the bottle upright and push the tip of the oral
dosing syringe firmlyinto the plastic adapter.

Step 7.Hold the syringe in place and carefully turn the bottle
upside down.

Step 8.Slowly pull down the plunger to fill the oral dosing
syringe slightly past your prescribed dose line to help
remove any air bubbles.

Step 9.Tap oral dosing syringe to move air bubbles to the
top. Doing this helps set the correct dose.

Step 10.Push the plunger back slowly just far enough to
completely push out any large or small air bubbles
that may be trapped in the oral dosing syringe.

Step 11.Slowly pull the plunger down until the top edge of the
plunger is level with the marker on the syringe barrel
for the prescribed dose.
Note:If the prescribed dose is more than 10 mL, you
will need to refill the oral dosing syringe to make up the
full dose.

Step 12.Carefully turn the bottle upright. Take out the oral
dosing syringe by gently twisting it out of the plastic
adapter. The plastic adapter should stay in the bottle.

Taking the dose of RALDESY oral solution

Note: Sit up straight while taking RALDESY.

Step 13.Place the oral dosing syringe gently into your mouth.
Push the plunger slowlyuntil the plunger moves all of
the medicine out of the oral dosing syringe.

Step 14.Swallow all of the medicine.

Step 15.Close the bottle by screwing the child-resistant cap
back on the bottle after use. Make sure the child-
resistant cap is tightly closed

Step 16. Cleaning:After use, rinse the oral dosing syringe with warm water and allow it to dry thoroughly.

Step 17. Throw away (discard):Safely throw away medicine that is expired or no longer needed. Do not throw away any medicine down the
sink or in your household trash. Ask your pharmacist how to throw away medicines you no longer use.

Storing RALDESY

- Store RALDESY at room temperature between 68°F to 77°F (20°C to 25°C).
- RALDESY comes in a bottle with a child-resistant cap.
- Keep RALDESY out of the light.
- Throw away (discard) RALDESY 20 days after first opening the bottle.
- Safely throw away medicine that is out of date or no longer needed.

Keep RALDESY and all medicines out of the reach of children.

Manufactured for and distributed by:

Validus Pharmaceuticals LLC

Parsippany, NJ 07054

This Instructions for Use has been approved by the U.S. Food and Drug Administration.

Approved: 04/2025

Rev. 03, 08/2025

PACKAGE LABEL PRINCIPAL DISPLAY PANEL

RALDESYTM(trazodone hydrochloride) Oral Solution 10 mg/mL - NDC 30698-455-02 - 150 mL Carton Label

RALDESYTM(trazodone hydrochloride) Oral Solution 10 mg/mL - NDC 30698-455-02 - 150 mL Bottle Label

RALDESYTM(trazodone hydrochloride) Oral Solution 10 mg/mL - NDC 30698-455-03 - 150 mL amber glass Carton Label

RALDESYTM(trazodone hydrochloride) Oral Solution 10 mg/mL - NDC 30698-455-03 - 150 mL amber glass Bottle Label

RALDESYTM(trazodone hydrochloride) Oral Solution 10 mg/mL - NDC 30698-455-04 - 300 mL amber glass Carton Label

RALDESYTM(trazodone hydrochloride) Oral Solution 10 mg/mL - NDC 30698-455-04 - 300 mL amber glass Bottle Label

RALDESYTM(trazodone hydrochloride) Oral Solution 10 mg/mL - NDC 30698-455-01 - 300 mL Carton Label

RALDESYTM(trazodone hydrochloride) Oral Solution 10 mg/mL - NDC 30698-455-01 - 300 mL Bottle Label